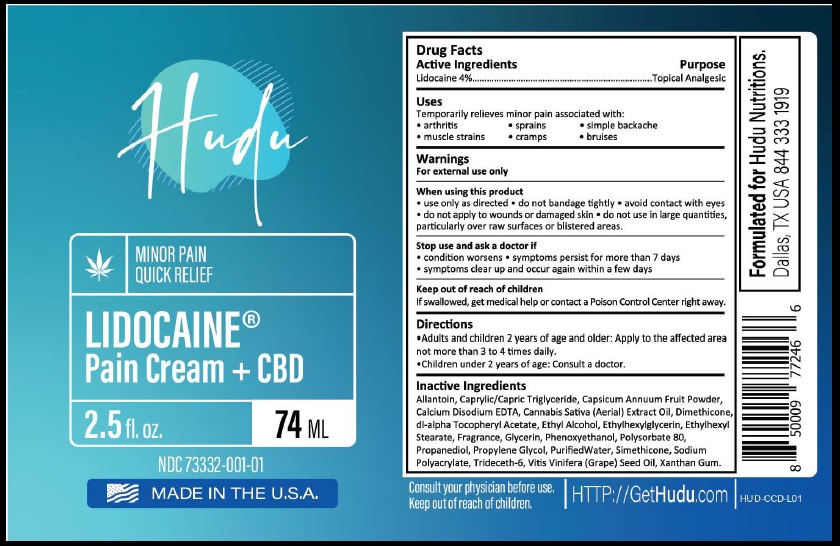 DRUG LABEL: CBD pain cream
NDC: 73332-001 | Form: CREAM
Manufacturer: NATURES ORGANICS LLC
Category: otc | Type: HUMAN OTC DRUG LABEL
Date: 20191010

ACTIVE INGREDIENTS: LIDOCAINE 40 mg/1 mL
INACTIVE INGREDIENTS: ALLANTOIN; TRICAPRIN; PAPRIKA; EDETATE CALCIUM DISODIUM ANHYDROUS; CANNABIS SATIVA SEED; DIMETHICONE; .ALPHA.-TOCOPHEROL ACETATE, DL-; ALCOHOL; ETHYLHEXYLGLYCERIN; ETHYLHEXYL STEARATE; GLYCERIN; PHENOXYETHANOL; POLYSORBATE 80; PROPANEDIOL; PROPYLENE GLYCOL; WATER; SODIUM POLYACRYLATE (2500000 MW); TRIDECETH-6; GRAPE SEED OIL; XANTHAN GUM

Drug Facts

Active Ingredient

Lidocaine 4%

Purpose

Topical analgesic

Uses

Temporarily relieves minor pain associated with:

.Arthritis .Sprains .Simple backache

.Bruises .Muscle strains .Cramps

Warnings

For external use only

When using this product

- Use only as directed, do not bandage tightly, avoid contact with eyes, do not apply to wounds or damaged skin, do not use in large quantities, particularly over raw surfaces or blistered areas.

Stop use and ask a doctor if

- condition worsens, symptoms persist for more than 7 days or symptoms clear up and occur again within a few days.

Keep out of reach of children

If swallowed, get medical help or contact a Poison Control Center right away

Directions

- Adults and children 12 years of age and older: apply to the affected area not more than 3 to 4 times daily.
- Children under 12 years of age : Consult a doctor

Inactive ingrdients

Allantoin, Caprylic/Capric Triglyceride, Capsicum Annuum Fruit Powder, Calcium Disodium EDTA, Cannabis Sativa Extract Oil, Dimethicone, dI-alpha Tocopheryl Acetate, Ethyl Alcohol, Ethylhexylglycerin, Ethylhexyl Sterate, Fragrance, Glycerin, Phenoxyethanol, Polysorbate 80, Propanediol, Propylene Glycol, Purified Water, Simethicone, Sodium Polyacrylate, Trideceth-6, Vitis Vinifera (Grape) Seed oil, Xanthan Gum.

Principal Display Panel

NDC 73332-001-01

FOR EXTERNAL USE ONLY

CBD Pain Cream

+ Lidocaine